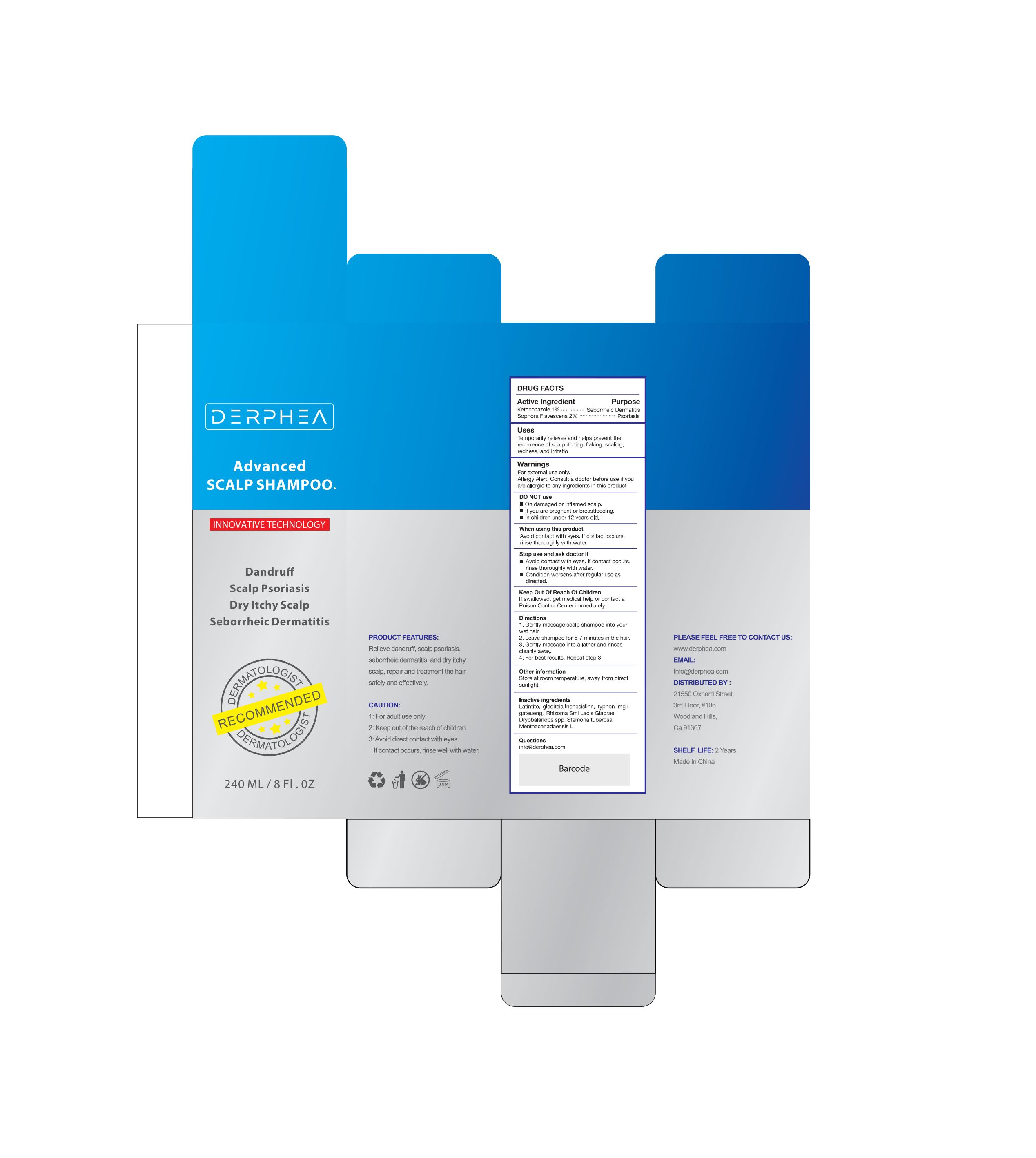 DRUG LABEL: DERPHEA Advanced Scalp Shampoo.
NDC: 83887-005 | Form: SHAMPOO
Manufacturer: Changsha Beiliang E-commerce Co., Ltd
Category: otc | Type: HUMAN OTC DRUG LABEL
Date: 20250219

ACTIVE INGREDIENTS: SOPHORA FLAVESCENS ROOT 2 g/100 mL; KETOCONAZOLE 1 g/100 mL
INACTIVE INGREDIENTS: STEMONA TUBEROSA WHOLE; SMILAX GLABRA TUBER; DRYOBALANOPS AROMATICA WHOLE; GLEDITSIA TRIACANTHOS WHOLE; BASSIA SCOPARIA FRUIT; MENTHA CANADENSIS WHOLE

83887-005

Active Ingredient

Sophora Flvescens 2%
Stemona tuberosa 1%

Purpose

Seborrheic dermatitis,PsoriasisAnti-fungal, Anti itchy

Use

Temporarily relieves and helps prevent the recurrence of scalp itching, flaking, scaling, redness, and irritation associated with psoriasis and seborrheic dermatitis.

Warnings

For external use only.
Allergy Alert: Consult a doctor before use if you are allergic to any ingredients in this product.

Do not use

On damaged or inflamed scalp.
If you are pregnant or breastfeeding.
In children under 12 years old.

When Using

Avoid contact with eyes. If contact occurs, rinse thoroughly with water.

Stop Use

Condition worsens or does not improve after regular use as directed.

Ask Doctor

Condition worsens after regular use as directed.

Keep Oot Of Reach Of Children

If swallowed, get medical help or contact a Poison Control Center immediately.

Directions

1 Gently massage scalp shampoo into your wet hair.
2 Leave shampoo for 5-7 minutes in the hair.
3 Gently massage into a lather and rinses cleanly away.
4 For best results, Repeat step 3.

Other information

Store at room temperature, away from directsunlight.

Inactive ingredients

Latintite
gleditsia Inenesislinn
typhon Img i gateueng
Rhizoma Smi Lacis Glabrae
Dryobalanops spp
Stemona tuberosa
Menthacanadaensis L

Questions

info@derphea.com